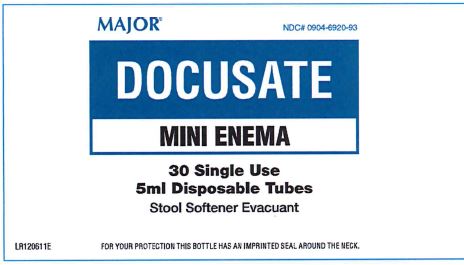 DRUG LABEL: Docusate Mini Enema
NDC: 0904-6920 | Form: LIQUID
Manufacturer: Major Pharmaceuticals
Category: otc | Type: HUMAN OTC DRUG LABEL
Date: 20251204

ACTIVE INGREDIENTS: DOCUSATE SODIUM 283 mg/5 mL
INACTIVE INGREDIENTS: POLYETHYLENE GLYCOL 300; GLYCERIN

MAJOR®
DOCUSATE
MINI ENEMA
30 Single Use
5 mL Disposable Tubes
Stool Softener Evacuant

Drug Facts

Active Ingredient (per delivered-dose)

Docusate Sodium USP 283 mg

Purpose

Stool Softener Laxative

Uses

- For relief of occasional constipation (irregularity).
- This product generally produces a bowel movement in 2 to 15 minutes.

Warnings

For rectal use only. Drug Interaction Precaution: Do not take this product if you are presently taking mineral oil, unless directed by a doctor.

Do not use

- Laxative products when abdominal pain, nausea or vomiting are present.
- Laxative products for a period longer than 1 week unless directed by a doctor.

Stop use and ask a doctor if you:

- Rectal bleeding.
- Noticed a sudden change in bowel habits that persists over a period of 2 weeks.
- Failed to have a bowel movement after use. This may indicate a serious condition.

Pregnant or Lactating Women

Ask a healthcare professional before use.

Keep out of reach of children

In case of accidental ingestion, get medical help or contact a Poison Control Center immediately.

Directions

Adults and children 12 years of age and older (with adult supervision) one to three units daily. Children under 12 years of age, consult a doctor prior to use.

- Twist off and remove tip.
- Lubricate tip prior to insertion: Place a few drops of the tube's liquid content on the shaft prior to insertion. Also apply liquid content or lubricant to the anus before inserting the mini-enema.
- Positioning: For best results, lay on the left side with knees bent. Insert slowley into rectum, up to shoulder of tube. Alternate Positions: Administer while seated on the toilet. Or, kneel, then lower head and chest forward until side of face is resting on the surface.
- With steady pressure, gently insert the tube into the rectum with care to prevent damage to the rectal wall. Squeeze to empty the contents. Keep the tube squeezed until it is removed from the rectum. After the contents have been emptied, remove the disposable tube and discard. A small amount of liquid may remain in the unit after use.

Other Information

Other Information Store at room temperature 15°-30° C (59°-86° F)

RETAIN BOTTLE FOR COMPLETE DRUG FACTS

Inactive Ingredients

Glycerin USP and Polyethylene Glycol

Questions or Comments: (800) 616-2471